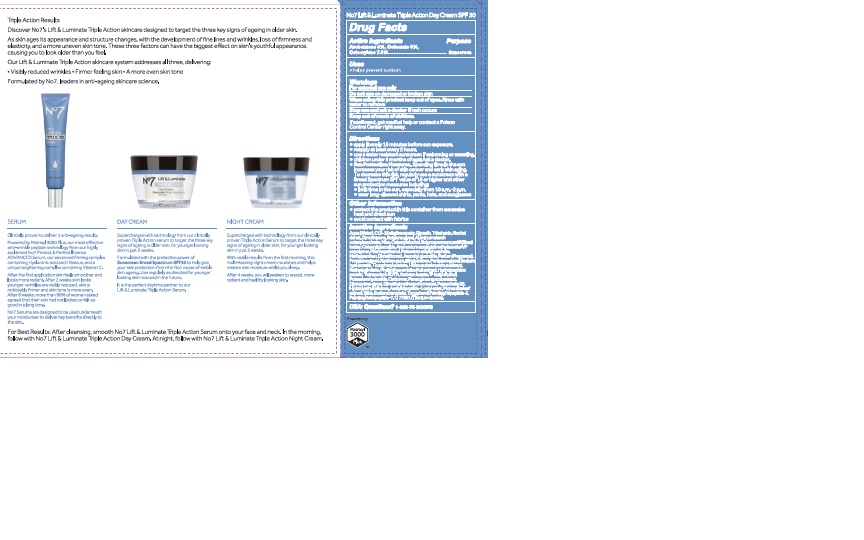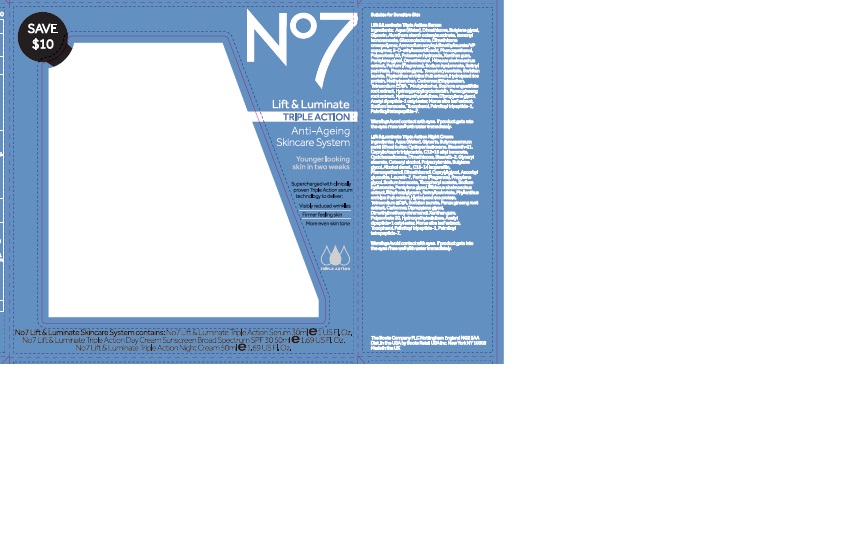 DRUG LABEL: No7 Lift and Luminate Triple Action Day Cream SPF 30
NDC: 11489-125 | Form: CREAM
Manufacturer: BCM Ltd
Category: otc | Type: HUMAN OTC DRUG LABEL
Date: 20170731

ACTIVE INGREDIENTS: AVOBENZONE 1.5 g/50 g; OCTOCRYLENE 3.75 g/50 g; OCTISALATE 2.5 g/50 g
INACTIVE INGREDIENTS: WATER; GLYCERIN; ALUMINUM STARCH OCTENYLSUCCINATE; DIMETHICONE; MICA; ALKYL (C12-15) BENZOATE; CETEARYL GLUCOSIDE; TRIBEHENIN; PENTYLENE GLYCOL; AMMONIUM ACRYLOYLDIMETHYLTAURATE/VP COPOLYMER; PHENOXYETHANOL; CETOSTEARYL ALCOHOL; SHEA BUTTER; BUTYLENE GLYCOL; METHYLPARABEN; DIMETHICONOL (40 CST); ETHYLPARABEN; XANTHAN GUM; SODIUM LAUROYL LACTYLATE; PHYLLANTHUS EMBLICA FRUIT; VITAMIN A PALMITATE; PANAX GINSENG ROOT WATER; ASCORBYL GLUCOSIDE; EDETATE SODIUM; TERT-BUTYL ALCOHOL; PROPYLENE GLYCOL; POLYSORBATE 20; CARBOMER 940; DIPROPYLENE GLYCOL; DIMETHYLMETHOXY CHROMANOL; POTASSIUM HYDROXIDE; N-ACETYL DIPEPTIDE-1; TOCOPHEROL; MORUS ALBA LEAF; SODIUM BENZOATE; TITANIUM DIOXIDE; PALMITOYL TETRAPEPTIDE-7; PALMITOYL TRIPEPTIDE-1

No7 Lift and Luminate Triple Action Day Cream Sunscreen Broad Spectrum SPF 30(component in No7 Lift and Luminate Triple Action Anti-Ageing Skincare System)

Carton Active Ingredients Section

Active ingredients

Avobenzone 3%

Octisalate 5%

Octocrylene 7.5%

Uses

Uses - helps prevent sunburn

Warnings

For external use only

Do not use on damaged or broken skin

When using this product keep out of eyes. Rinse with water to remove.

Ask a doctor

Stop use and ask a doctor if rash occurs

Keep out of reach of children

If swallowed, get medical help or contact a Poison Control Center right away

Directions

Apply liberally 15 minutes before sun exposure

reapply at least every 2 hours

use a water resistant sunscreen if swimming or sweating

children under 6 months of age: Ask a doctor

Sun Protection Measures. Spending time in the sun increases your risk of skin cancer and early skin aging.

To decrease this risk, regularly use a sunscreen with a Broad Spectrum SPF value of 15 or higher and other sun protection measures including:

Limit time in the sun, especially from 10 a.m - 2 p.m.

wear long-sleeved shirts,pants,hats and sunglasses.

Storage

Other information

Protect the product in this container from excessive heat and direct sun

Avoid contact with fabrics

Inactive ingredients

Aqua(Water), Glycerin, C12-15 alkyl bezoate, Butyrospermum parkii (Shea) butter, Isostearyl isostearate, Cyclopentasiloxane, Dimethicone, Cyclohexasiloxane, Glyeryl stearate, Tribehenin, Cetearyl alcohol, PEG-100 stearate, Ammonium acryloyldimethyltaurate/VP copolymer, Silica, Phenoxyethanol, Myristyl myristate, Rosa canina fruit oil, Dimethiconol, Butylene glycol, Methylparaben, Parfum(Fragrance), Xanthan gum, Ethylparaben, Sodium lauroyl lactylate, Ascorbyl glucoside, Retinyl palmitate, Diospyros kaki calyx extract, Cholesterol, Tetrasodium EDTA, T-butyl alcohol, Lupinus albus seed extract, Propylene glycol, Carbomer, Potassium hydroxide, Ceramide 3, Ethylhexylglycerin, Polysorbate 20, Ceramide 6 ll, Phytosphingosine, Tocopherol, Triethyl citrate, Palmitoyl tripeptide-1, Palmitoyl tetrapeptide-7, Ceramide 1, CI77891(Titanium dioxide) CI 77491(Iron oxides), CI14700(Red 4)

PATIENT COUNSELING INFORMATION

The Boots Company PLC Nottingham England NG2 3AA

Dist in the USA by Boots Retail USA Inc. New York NY 10005

Made in the UK

www.boots.com

Description

No7 Lift and Luminate Triple Action Anti-Ageing Skincare System.

Younger looking skin in two weeks

Supercharged with clinically proven Triple Action serum technology to deliver:

Visibly reduced wrinkles

Firmer feeling skin

More even skin tone

No7 Lift and Luminate Skincare System contains: No7 Lift and Luminate Triple Action Serum 30ml e 1 US Fl.Oz. No7 Lift and Luminate Triple Action Day Cream Sunscreen Broad Spectrum SPF 30 50ml e 1.69 US Fl.Oz. No7 Lift and Luminate Triple Action Night Cream 50ml e 1.69 US Fl.Oz.

Description section

Triple Action Results

Discover No7's Lift and Luminate Triple Action skincare designed to target the three key signs of ageing in older skin.

As skin ages its appearance and structure changes, with the development of fine lines and wrinkles, loss of firmness and elasticity, and a more uneven skin tone. These three factors can have the biggest effect on skin's youthful appearance, causing you to look older than you feel.

Our Lift and Luminate Triple Action skincare system addresses all three, delivering:

Visibly reduced wrinkles - Firmer feeling skin - A more even skin tone

Formulated by No7, leaders in anti-ageing skincare science.

SERUM

Clinically proven to deliver 3 anti-ageing results.

Powered by Matrixyl 3000 Plus, our most effective anti-wrinkle peptide technology, from our highly acclaimed No7 Protect and Perfect Intense Advanced Serum, our advanced firming complex containing Hyaluronic acid and Hibiscus, and a unique brightening complex containing Vitamin C.

After the first application skin feels smoother and looks more radiant. after 2 weeks skin looks younger:wrinkles are visibly reduced, skin is noticeably firmer and skin tone is more even. After 8 weeks, more than 80% of women asked agreed that their skin had not looked or felt so good in a long time.

No7 Serums are designed to be used underneath your moisturiser to deliver key benefits directly to the skin.

DAY CREAM

Supercharged with technology from our clinically proven Triple Action serum to target the three key signs of ageing in older skin, for younger looking skin in just 2 weeks.

Formulated with the protective power of Sunscreen Broad Spectrum SPF 30 to help give your skin protection from the No1 cause of visible skin ageing. Use regularly as directed for younger looking skin now and in the future.

It is the perfect daytime partner to our Lift and Luminate Triple Action Serum.

NIGHT CREAM

Supercharged with technology from our clinically proven Triple Action Serum to target the three key signs of ageing in older skin, for younger looking skin in just 2 weeks.

With visible results from the first morning, this multi-tasking night cream nourishes and helps restore skin moisture whilst you sleep.

After 4 weeks, you will awaken to rested, more radiant and healthy looking skin.

For Best results: After cleansing, smooth No7 Lift and Luminate Triple Action Serum onto your face and neck. In the morning, follow with No7 Lift and Luminate Triple Action Day Cream. At night, follow with No7 Lift and Luminate Triple Action Night Cream